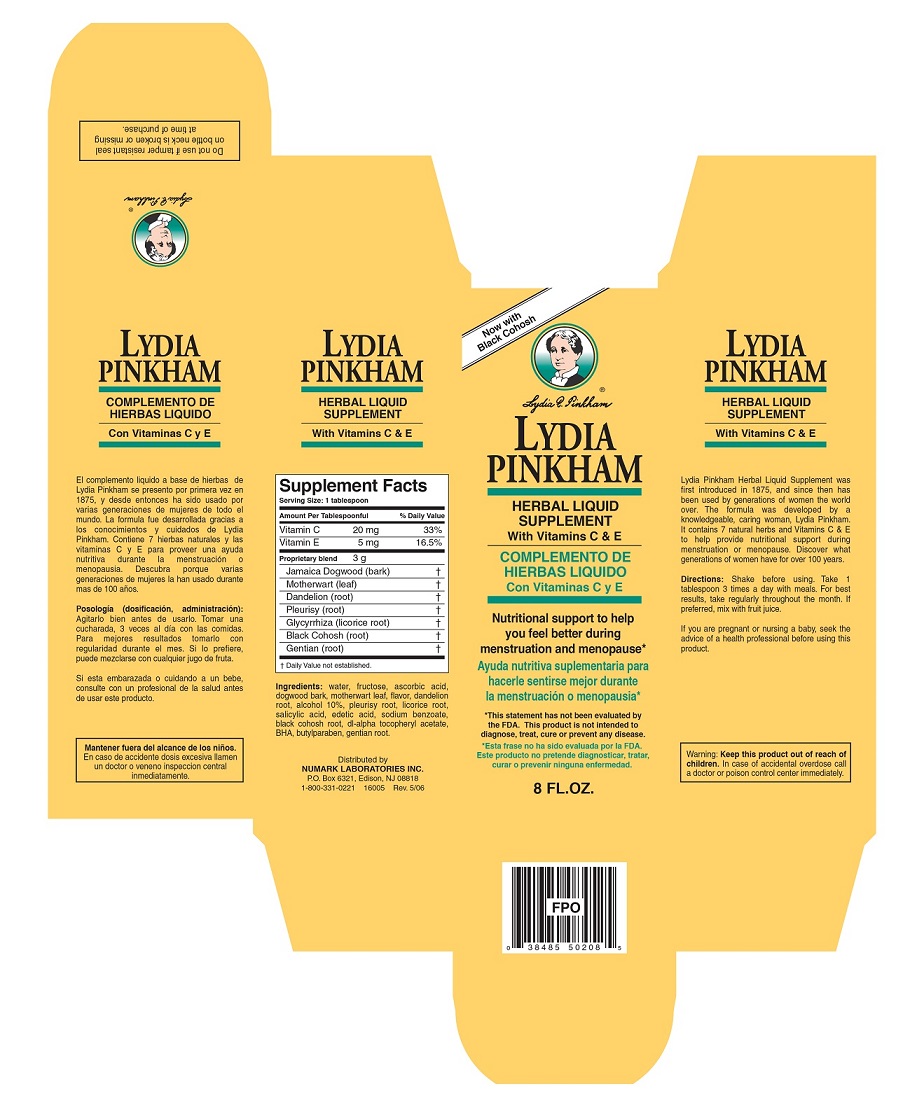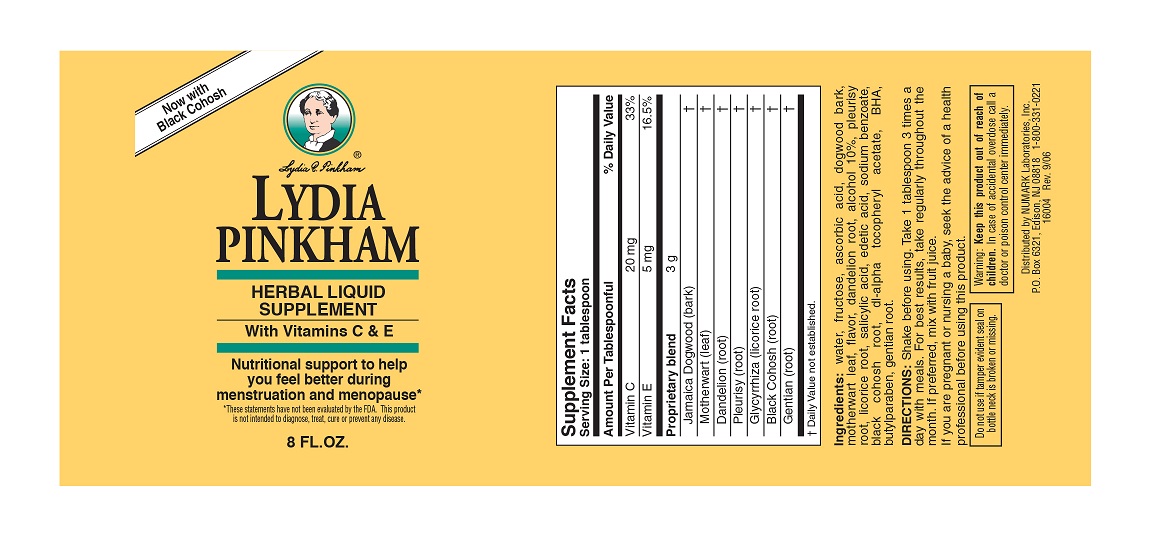 DRUG LABEL: LYDIA PINKHAM Herbal Supplement 
NDC: 69846-502 | Form: LIQUID
Manufacturer: NUMARK BRANDS, INC
Category: other | Type: DIETARY SUPPLEMENT
Date: 20160812

ACTIVE INGREDIENTS: Ascorbic Acid 1.33 mg/1 mL; .alpha.-tocopherol Acetate, Dl- .33 mg/1 mL
INACTIVE INGREDIENTS: Water; Fructose; Piscidia Piscipula Root Bark 1 mg/1 mL; Taraxacum Officinale Root; Alcohol; Asclepias Tuberosa Root; Licorice; Salicylic Acid; Edetic Acid; Sodium Benzoate; Black Cohosh; Butylated Hydroxyanisole; Butylparaben; Gentiana Lutea Root

LYDIA PINKHAM HERBAL LIQUID SUPPLEMENT With Vitamins C & E
LYDIA PINKHAM COMPLEMENTO DE HIERBAS LIQUIDO Con Vitaminas C y E

Supplement Facts

Serving Size: 1 tablespoon

Amount Per Tablespoonful |  | % Daily Value
Vitamin C | 20 mg | 33%
Vitamin E | 5 mg | 16.5%
Proprietary blend | 3 g | †
Jamaica Dogwood (bark) |  | †
Motherwart (leaf) |  | †
Dandelion (root) |  | †
Pleurisy (root |  | †
Glycyrrhiza (licorice root) |  | †
Black Cohosh (root |  | †
Gentian (root) |  | †
† Daily Value not established

Ingredients: water, fructose, ascorbic acid, dogwood bark, motherwart leaf, flavor, dandelion root, alcohol 10%, pleurisy root, licorice root, salicylic acid, edetic acid, sodium benzoate, black cohosh root, dl-alpha tocopheryl acetate, BHA, butylparaben, gentian root.

Directions:

Shake before using. Take 1 tablespoon 3 times a day with meals. For best results, take regularly throughout the month. If preferred, mix with fruit juice.

Posología, (dosificación, administración):

Agitarlo bien antes de usarlo. Tomar una cucharada, 3 veces al día con las comidas. Para mejores resultados tomarlo con regularidad durante el mes. Si lo prefiere, puede mezclarse con cualquier jugo de fruta.

PRECAUTIONS

If you are pregnant or nursing a baby, seek the advice of a health professional before using this product.

PRECAUTIONS

Si esta embarazado o cuidando a un bebe, consulte con un professional de la salud antes de usar este producto.

HEALTH CLAIM

Nutritional support to help you feel better during menstruation and menopause*

* This statement has not been evaluated by the FDA. This product is not intended to diagnose, treat, cure or prevent any disease.

Lydia Pinkham Herbal Liquid Supplement was first introduced in 1875, and since then has been used by generations of women the world over. The formula was developed by a knowledgeable, caring woman, Lydia Pinkham. It contains 7 natural herbs and Vitamins C & E to help provide nutritional support during menstruation or menopause. Discover what generations of women have for over 100 years.

HEALTH CLAIM

Ayuda nutritiva suplementaria para hacerle sentirse mejor durante la menstruación o menopausia*

* Esta frase no ha sido evaluada por la FDA. Este producto no pretende diagnosticar, trartar, curar o prevenir ninguna enfermedad.

El complemento liquido a base de hierbas de Lydia Pinkham se presento por primera vez en 1875, y desde entonces ha sido usado por varias generaciones de mujeres de todo el mundo. La formula fue desarrollada gracias a los conocimientos y cuidados de Lydia Pinkham. Contiene 7 hierbas naturales y las vitaminas C y E para proveer una ayuda nutritiva durante la menstruación o menopausia. Descubra porque varias generaciones de mujeres la han usado durante mas de 100 años.

WARNINGS

Warning: Keep this product out of reach of children. In case of accidental overdose call a doctor or poison control center immediately.

WARNINGS

Mantener fuera del alcance de los niños. En caso de accidente dosis excesiva llamen un doctor o veneno inspeccion central inmediatamente.

PRINCIPAL DISPLAY PANEL

Now with Black Cohosh
LYDIA PINKHAM
HERBAL LIQUID SUPPLEMENT
With Vitamins C & E
COMPLEMENTO DE HIERBAS LIQUIDO
Con Vitaminas C y E
8 FL.OZ.
Distributed by
NUMARK LABORATORIES INC.
P.O. Box 6321, Edison, NJ 08818
1-800-331-0221 16005 Rev. 5/06
Do not use if tamper resistant seal on bottle neck is broken or missing at time of purchase.

Now with Black Cohosh
LYDIA PINKHAM
HERBAL LIQUID SUPPLEMENT
With Vitamins C & E
8 FL.OZ.
Do not use if tamper resistant seal on bottle neck is broken or missing at time of purchase.
Distributed by NUMARK Laboratories, Inc.
P.O. Box 6321, Edison, NJ 08818 1-800-331-0221
16004 Rev 9/06